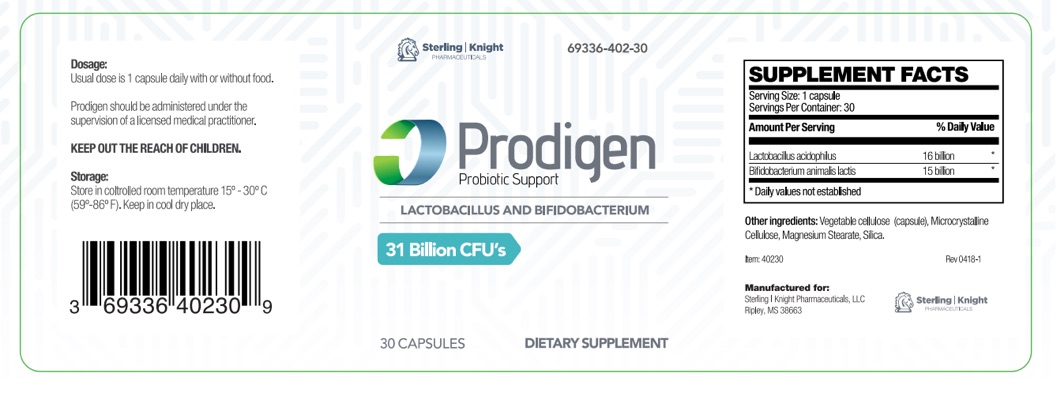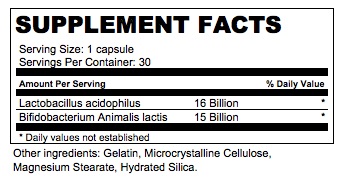 DRUG LABEL: Prodigen
NDC: 69336-402 | Form: CAPSULE
Manufacturer: Sterling Knight Pharmaceuticals LLC
Category: other | Type: DIETARY SUPPLEMENT
Date: 20180731

ACTIVE INGREDIENTS: LACTOBACILLUS ACIDOPHILUS 16000000000 [CFU]/1 1; BIFIDOBACTERIUM ANIMALIS LACTIS 15000000000 [CFU]/1 1
INACTIVE INGREDIENTS: MICROCRYSTALLINE CELLULOSE; MAGNESIUM STEARATE; HYDRATED SILICA

Prodigen Capsules
Dietary Supplement

HEALTH CLAIM:

Prodigen Capsules Dietary Supplemement

Dispensed by Prescription†

DESCRIPTION

Prodigen is an orally administered prescription probiotic formulation for the clinical dietary management of suboptimal nutritional status in patients where advanced supplementation is required and nutritional supplementation in physiologically stressful conditions for maintenance of good health is needed.

Prodigen should be administered under the supervision of a licensed medical practitioner.

WARNINGS AND PRECAUTIONS

This product is contraindicated in patients with a known hypersensitivity to any of the ingredients.

Prodigen should only be used under the direction and supervision of a licensed medical practitioner. Use with caution in patients that may have a medical condition, are pregnant, lactating, trying to conceive, under the age of 18, or taking medications.

DOSAGE AND ADMINISTRATION

Usual adult dose is 1 capsule daily with or without food.

INDICATIONS AND USAGE

Prodigen is an orally administered prescription probiotic formulation for the clinical dietary management of suboptimal nutritional status in patients where advanced supplementation is required and nutritional supplementation in physiologically stressful conditions for maintenance of good health is needed.

HOW SUPPLIED:

Prodigen is supplied as clear capsules dispensed in HDPE plastic bottles of 30ct.

69336-402-30

Reserved for Professional Recommendation
All prescriptions using this product shall be pursuant to state statutes as applicable. This is not an Orange Book product. This product may be administered only under a physician’s supervision. There are no implied or explicit claims on therapeutic equivalence.
Manufactured for:
Sterling-Knight Pharmaceuticals, LLC
Ripley, MS 38663

Item 40230
Rev. 0418-1

STORAGE:

Store at controlled room temperature 15°-30°C (59°F-86°F). Keep in cool dry place. Call your doctor about side effects. You may report side effects to FDA at 1-800-FDA-1088.

KEEP THIS OUT OF THE REACH OF CHILDREN.